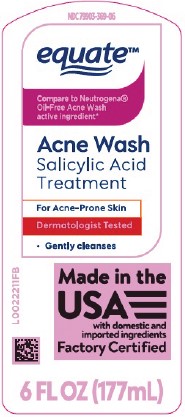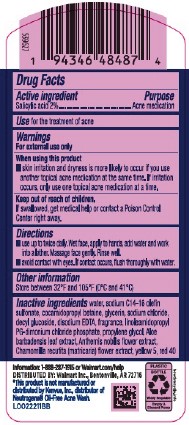 DRUG LABEL: Oil Free Acne Wash
NDC: 79903-369 | Form: LOTION
Manufacturer: Walmart Inc.
Category: otc | Type: HUMAN OTC DRUG LABEL
Date: 20260227

ACTIVE INGREDIENTS: SALICYLIC ACID 20 mg/1 mL
INACTIVE INGREDIENTS: WATER; SODIUM C14-16 OLEFIN SULFONATE; COCAMIDOPROPYL BETAINE; GLYCERIN; SODIUM CHLORIDE; DECYL GLUCOSIDE; EDETATE DISODIUM; LINOLEAMIDOPROPYL PROPYLENE GLYCOL-DIMONIUM CHLORIDE PHOSPHATE; PROPYLENE GLYCOL; ALOE VERA LEAF; CHAMAEMELUM NOBILE FLOWER; CHAMOMILE; FD&C YELLOW NO. 5; FD&C RED NO. 40

Equate 947.003/947AC-AD
Oil Free Acne Wash

Active Ingredient

Salicylic acid 2%

PURPOSE

Acne medication

Use

for the treatment of acne

Warnings

For external use only

When using this product

- skin irritation and dryness is more likely to occur if you use another topical acne medication at the same time. If irritation occurs, only use one topical acne medication at a time.

Keep out of reach of children.

If swallowed, get medical help or contact a Poison Control Center right away.

Directions

- use up to twice daily. Wet face, apply to hands, add water and work into a lather. Massage face gently. Rinse well.
- avoid contact with eyes. If contact occurs, flush thoroughly with water.

Other information

Store between 32°F and 105°F (0°C and 41°C)

Inactive ingredients

water, sodium C14-16 olefin sulfonate, cocamidopropyl betaine, glycerin, sodium chloride, decyl glucoside, disodium EDTA, fragrance, linoleamidopropyl PG-dimonium chloride phosphate, propylene glycol, Aloe barbadensis leaf extract, Anthemis nobilis flower extract, Chamomilla recutita (matricaria) flower extract, yellow 5, red 40

Disclaimer

*This product is not manufactured or distributed by Kenvue, Inc., distributor of Neutrogena® Oil Free Acne Wash.

ADVERSE REACTION

Information: 1-888-287-1915 or Walmart.com/help

DISTRIBUTED BY: Walmart Inc., Bentonville, AR 72716

Empty & Discard Pump

Widely Recyclable

PLASTIC BOTTLE

how2recycle.info

PRINCIPAL DISPLAY PANEL

NDC 79903-369-06

equate™

Compare to Neutrogena® Oil-Free Acne Wash Active Ingredient*

Acne Wash

Salicylic acid treatment

For Acne-Prone Skin

Dermatologist Tested

- Gently cleanses

Made in the USA with domestic and imported ingredients

Factory Certified

6 FL OZ (177 mL)